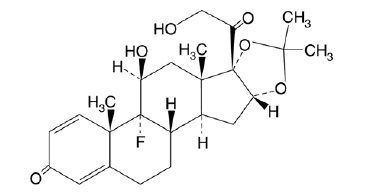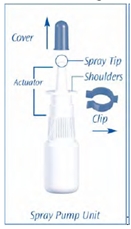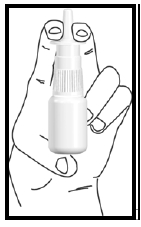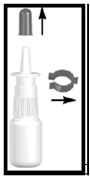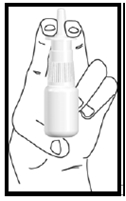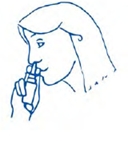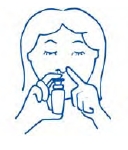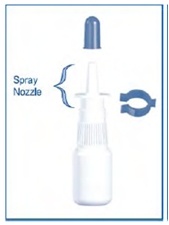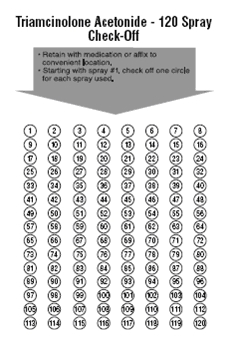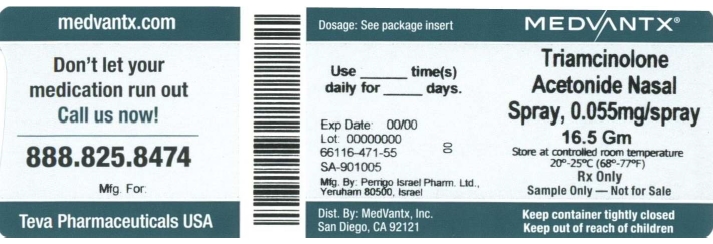 DRUG LABEL: Triamcinolone Acetonide
NDC: 66116-471 | Form: SPRAY, METERED
Manufacturer: MedVantx, Inc.
Category: prescription | Type: HUMAN PRESCRIPTION DRUG LABEL
Date: 20110406

ACTIVE INGREDIENTS: TRIAMCINOLONE ACETONIDE 55 ug/1 1
INACTIVE INGREDIENTS: BENZALKONIUM CHLORIDE; CARBOXYMETHYLCELLULOSE SODIUM; ANHYDROUS DEXTROSE; EDETATE DISODIUM; CELLULOSE, MICROCRYSTALLINE; POLYSORBATE 80; HYDROCHLORIC ACID; SODIUM HYDROXIDE

HIGHLIGHTS OF PRESCRIBING INFORMATION

These highlights do not include all the information needed to use Triamcinolone Acetonide Nasal Spray safely and effectively. See full prescribing information for Triamcinolone Acetonide Nasal Spray.
Triamcinolone Acetonide Nasal Spray
For intranasal use only. Shake Well Before Using.
Initial U.S. Approval: 1957

1 INDICATIONS AND USAGE

- Triamcinolone Acetonide Nasal Spray is a corticosteroid indicated for treatment of nasal symptoms of seasonal and perennial allergic rhinitis in adults and children 6 years of age and older. (1)

2 DOSAGE AND ADMINISTRATION

- Adults and adolescents ≥12 years: Starting and maximum dose is 220 mcg/day (two sprays in each nostril once daily). (2.1)
- Children 6 to 12 years of age: Starting dose is 110 mcg/day (one spray in each nostril once daily). Maximum dose is 220 mcg/day (two sprays per nostril once daily). (2.2)
- Priming/Use: Shake well before each use. Before using for the first time, release 5 sprays into the air away from the face. If the product is not used for more than 2 weeks, release 1 spray into the air before using. (2.3)

3 DOSAGE FORMS AND STRENGTHS

- Nasal Spray: 55 mcg triamcinolone acetonide in each spray. Supplied in 16.5 g bottle containing 120 actuations. Each 120 actuation bottle contains 9.075 mg triamcinolone acetonide. (3)

4 CONTRAINDICATIONS

- Do not administer to patients with history of hypersensitivity to triamcinolone acetonide or any ingredients of this product. (4)

5 WARNINGS AND PRECAUTIONS

- Epistaxis, nasal septal perforation, Candida albicans infection, impaired wound healing. Monitor patients periodically for signs of adverse effects on the nasal mucosa. Avoid use in patients with recent nasal septal ulcers, nasal surgery, or trauma. (5.1)
- Development of glaucoma or posterior subcapsular cataracts. Monitor patients closely with a change in vision or with a history of increased intraocular pressure, glaucoma, and/or cataracts. (5.2)
- Potential worsening of existing tuberculosis; fungal, bacterial, viral, or parasitic infections; or ocular herpes simplex. More serious or even fatal course of chickenpox or measles in susceptible patients. Use caution in patient with the above because of the potential for worsening of these infections. (5.3)
- Hypercorticism and adrenal suppression with very high dosages or at the regular dosage in susceptible individuals. If such changes occur, discontinue triamcinolone acetonide nasal spray slowly. (5.4)
- Potential reduction in growth velocity in children. Monitor growth routinely in pediatric patients receiving triamcinolone acetonide nasal spray. (5.5, 8.4)

6 ADVERSE REACTIONS

- Most common adverse reactions (>2% incidence) were pharyngitis, epistaxis, flu syndrome, cough increased, bronchitis, dyspepsia, tooth disorder, headache, pharyngolaryngeal pain, nasopharyngitis, abdominal upper pain, diarrhea, and excoriation. (6.1)
- Other adverse reactions, including serious adverse reactions, have been reported. (6.1)

To report SUSPECTED ADVERSE REACTIONS, contact TEVA USA, PHARMACOVIGILANCE at 1-888-838-2872 X6351 ordrug.safety@tevausa.com or FDA at 1-800-FDA-1088 or www.fda.gov/medwatch.

8 USE IN SPECIFIC POPULATIONS

Triamcinolone acetonide should be used during pregnancy only if potential benefit justifies potential risk to fetus. (8.1)

Labeling describing use of triamcinolone acetonide nasal spray in pediatric patients 2 to 5 years of age is approved for Sanofi-Aventis U.S. Inc.’s Nasacort® AQ Nasal Spray. However, due to Sanofi-Aventis U.S. Inc.’s marketing exclusivity rights, a description of that use is not approved for this triamcinolone acetonide nasal spray labeling.

FULL PRESCRIBING INFORMATION

1 INDICATIONS AND USAGE

Triamcinolone Acetonide Nasal Spray is indicated for the treatment of the nasal symptoms of seasonal and perennial allergic rhinitis in adults and children 6 years of age and older.

Labeling describing use of triamcinolone acetonide nasal spray in pediatric patients 2 to 5 years of age is approved for Sanofi-Aventis U.S. Inc.’s Nasacort® AQ Nasal Spray. However, due to Sanofi-Aventis U.S. Inc.’s marketing exclusivity rights, a description of that use is not approved for this triamcinolone acetonide nasal spray labeling.

2 DOSAGE AND ADMINISTRATION

Administer Triamcinolone Acetonide Nasal Spray by the intranasal route only. Shake Triamcinolone Acetonide Nasal Spray well before each use.

2.1 Adults and Adolescents 12 Years of Age and Older

The recommended starting and maximum dose is 220 mcg per day as two sprays in each nostril once daily. Titrate an individual patient to the minimum effective dose to reduce the possibility of side effects. When the maximum benefit has been achieved and symptoms have been controlled, reducing the dose to 110 mcg per day (one spray in each nostril once a day) has been shown to be effective in maintaining control of the allergic rhinitis symptoms.

2.2 Children 6 to 12 Years of Age

Children 6 to 12 years of Age

The recommended starting dose is 110 mcg per day given as one spray in each nostril once daily. Children not responding adequately to 110 mcg per day may use 220 mcg (2 sprays in each nostril) once daily. Once symptoms have been controlled, the dosage may be decreased to 110 mcg once daily.

Labeling describing additional dosing of triamcinolone acetonide nasal spray in pediatric patients 2 to 5 years of age is approved for Sanofi-Aventis U.S. Inc.’s Nasacort® AQ Nasal Spray. However, due to Sanofi-Aventis U.S. Inc.’s marketing exclusivity rights, a description of that dosing is not approved for this triamcinolone acetonide nasal spray labeling.

Triamcinolone Acetonide Nasal Spray is not recommended for children under 2 years of age.

2.3 Administration Information

Priming

Prime Triamcinolone Acetonide Nasal Spray before using for the first time by shaking the contents well and releasing 5 sprays into the air away from the face. It will remain adequately primed for two weeks. If the product is not used for more than 2 weeks, then it can be adequately reprimed with one spray. Shake Triamcinolone Acetonide Nasal Spray well before each use.

If adequate relief of symptoms has not been obtained after 3 weeks of treatment, Triamcinolone Acetonide Nasal Spray should be discontinued. [see Warnings and Precautions (5), Patient Counseling Information (17), and Adverse Reactions (6)]

3 DOSAGE FORMS AND STRENGTHS

Triamcinolone acetonide nasal spray is a metered-dose pump spray containing the active ingredient triamcinolone acetonide. Each actuation delivers 55 mcg triamcinolone acetonide from the nasal actuator after an initial priming of 5 sprays. Each 16.5 gram bottle (120 actuations) contains 9.075 mg of triamcinolone acetonide. The bottle should be discarded when the labeled- number of actuations have been reached even though the bottle is not completely empty.

4 CONTRAINDICATIONS

Triamcinolone acetonide should not be administered to patients with a history of hypersensitivity to triamcinolone acetonide or to any of the other ingredients of this preparation.

5 WARNINGS AND PRECAUTIONS

5.1 Local Nasal Effects

Epistaxis

In clinical studies of 2 to 12 weeks duration, epistaxis was observed more frequently in patients treated with triamcinolone acetonide nasal spray than those who received placebo [see Adverse Reactions (6)].

Nasal Septal Perforation

In clinical trials, nasal septum perforation was reported in one adult patient treated with triamcinolone acetonide nasal spray.

Candida Infection

In clinical studies with triamcinolone acetonide nasal spray, the development of localized infections of the nose and pharynx with Candida albicans has rarely occurred. When such an infection develops it may require treatment with appropriate local or systemic therapy and discontinuation of triamcinolone acetonide nasal spray. Therefore, patients using triamcinolone acetonide nasal spray over several months or longer should be examined periodically for evidence of Candida infection or other signs of adverse effects on the nasal mucosa.

Impaired Wound Healing

Because of the inhibitory effect of corticosteroids on wound healing, patients who have experience recent nasal ulcers, surgery, or trauma should not use triamcinolone acetonide nasal spray until healing has occurred.

5.2 Glaucoma and Cataracts

Nasal and inhaled corticosteroids may result in the development of glaucoma and/or cataracts. Therefore, close monitoring is warranted in patients with a change in vision or with a history of increased intraocular pressure, glaucoma and/or cataracts.

5.3 Immunosuppression

Persons who are using drugs that suppress the immune system are more susceptible to infections than healthy individuals. Chickenpox and measles, for example, can have a more serious or even fatal course in susceptible children or adults using corticosteroids. In children or adults who have not had these diseases or have not been properly immunized, particular care should be taken to avoid exposure. How the dose, route, and duration of corticosteroid administration affect the risk of developing a disseminated infection is not known. The contribution of the underlying disease and/or prior corticosteroid treatment to the risk is also not known. If exposed to chickenpox, prophylaxis with varicella zoster immune globulin (VZIG) may be indicated. If exposed to measles, prophylaxis with pooled intramuscular immunoglobulin (IG) may be indicated. (see the respective package inserts for complete VZIG and IG prescribing information.) If chickenpox develops, treatment with antiviral agents may be considered.

Corticosteroids should be used with caution, if at all, in patients with active or quiescent tuberculosis infections of the respiratory tract; untreated local or systemic fungal or bacterial infections; systemic viral or parasitic infections, or ocular herpes simplex because of the potential for worsening of these infections.

5.4 Hypothalamic-Pituitary-Adrenal Axis Effects

Hypercorticism and Adrenal Suppression

When intranasal steroids are used at higher than recommended dosages or in susceptible individuals at recommended dosages, systemic corticosteroid effects such as hypercorticism and adrenal suppression may appear. If such changes occur, the dosage of triamcinolone acetonide nasal spray should be discontinued slowly, consistent with accepted procedures for discontinuing oral corticosteroid therapy. The replacement of a systemic corticosteroid with a topical corticosteroid can be accompanied by signs of adrenal insufficiency. In addition, some patients may experience symptoms of corticosteroid withdrawal, e.g., joint and/or muscular pain, lassitude, and depression. Patients previously treated for prolonged periods with systemic corticosteroids and transferred to topical corticosteroids should be carefully monitored for acute adrenal insufficiency in response to stress. In those patients who have asthma or other clinical conditions requiring long-term systemic corticosteroid treatment, rapid decreases in systemic corticosteroid dosages may cause a severe exacerbation of their symptoms.

5.5 Effect on Growth

Corticosteroids may cause a reduction in growth velocity when administered to pediatric patients. Monitor the growth routinely of pediatric patients receiving triamcinolone acetonide nasal spray. To minimize the systemic effects of intranasal corticosteroids, including triamcinolone acetonide nasal spray, titrate each patient’s dose to the lowest dosage that effectively controls his/her symptoms [see Use in Specific Populations (8.4)].

6 ADVERSE REACTIONS

Systemic and local corticosteroid use may result in the following:

- Epistaxis, Candida albicans infection, nasal septal perforation, impaired wound healing [see Warnings and Precautions (5.1)]
- Glaucoma and Cataracts [see Warnings and Precautions (5.2)]
- Immunosuppression [see Warnings and Precautions (5.3)]
- Hypothalamic-pituitary-adrenal (HPA) axis effects, including growth reduction [see Warnings and Precautions (5.4, 5.5), Use in Specific Populations (8.4)]

6.1 Clinical Trials Experience

In placebo-controlled, double-blind, and open-label clinical studies, 1483 adults and children 12 years and older received treatment with triamcinolone acetonide nasal spray. These patients were treated for an average duration of 51 days. In the controlled trials (2-5 weeks duration) from which the following adverse reaction data are derived, 1394 patients were treated with triamcinolone acetonide nasal spray for an average of 19 days. In a long-term, open-label study, 172 patients received treatment for an average duration of 286 days. Adverse reactions from 12 studies in adults and adolescent patients 12 to 17 years of age receiving triamcinolone acetonide nasal spray 27.5 mcg to 440 mcg once daily are summarized in Table 1.

In clinical trials, nasal septum perforation was reported in one adult patient who received triamcinolone acetonide nasal spray.

Table 1 - Adverse drug reactions > 2% and greater than placebo with triamcinolone acetonide nasal spray 220 mcg treatment in studies in adults and adolescents 12 years and older
 | Placebo; (N=962) | Triamcinolone Acetonide; 220 mcg; (N=857)
Adverse reaction | % | %
Pharyngitis | 3.6 | 5.1
Epistaxis | 0.8 | 2.7
Cough increased | 1.5 | 2.1
Coding dictionary for adverse events is Coding Symbols for Thesaurus of Adverse Reaction Terms (COSTART).

A total of 602 children 6 to 12 years of age were studied in 3 double-blind, placebo-controlled clinical trials. Of these, 172 received 110 mcg/day and 207 received 220 mcg/day of triamcinolone acetonide nasal spray for two, six, or twelve weeks. The longest average durations of treatment for patients receiving 110 mcg/day and 220 mcg/day were 76 days and 80 days, respectively. One percent of patients treated with triamcinolone acetonide were discontinued due to adverse experiences. No patient receiving 110 mcg/day and one patient receiving 220 mcg/day discontinued due to a serious adverse event. A similar adverse reaction profile was observed in pediatric patients 6 to 12 years of age as compared to adolescents and adults with the exception of epistaxis which occurred in less than 2% of the children studied. Adverse reactions from 2 studies in children 4 to 12 years of age receiving triamcinolone acetonide nasal spray 110 mcg once daily are summarized in Table 2.

Table 2 - Adverse drug reactions > 2% and greater than placebo with triamcinolone acetonide nasal spray 110 mcg treatment in US studies in patients 4 to 12 years of age
 | Placebo; (N=202) | Triamcinolone Acetonide; 110 mcg; (N=179)
Adverse reaction | % | %
Flu syndrome | 7.4 | 8.9
Cough increased | 6.4 | 8.4
Pharyngitis | 6.4 | 7.8
Bronchitis | 1 | 3.4
Dyspepsia | 1 | 3.4
Tooth disorder | 1 | 3.4
Coding dictionary for adverse events is Coding Symbols for Thesaurus of Adverse Reaction Terms (COSTART).

Labeling describing adverse events of triamcinolone acetonide nasal spray in pediatric patients 2 to 5 years of age is approved for Sanofi-Aventis U.S. Inc.’s Nasacort® AQ Nasal Spray. However, due to Sanofi-Aventis U.S. Inc.’s marketing exclusivity rights, a description of those adverse events is not approved for this triamcinolone acetonide nasal spray labeling.

In the event of accidental overdose, an increased potential for these adverse experiences may be expected, but acute systemic adverse experiences are unlikely. [see Overdosage (10)]

6.2 Post-Marketing Experience

In addition to the adverse drug reactions reported during clinical studies and listed above, the following adverse events have been identified during post-approval use of triamcinolone acetonide nasal spray. Because these events are reported voluntarily from a population of uncertain size, it is not always possible to reliably estimate their frequency or establish a causal relationship to drug exposure. Events that have been reported during post-marketing experience include: nasal discomfort and congestion, sneezing, alterations of taste and smell, nausea, insomnia, dizziness, fatigue, dyspnea, decreased blood cortisol, cataract, glaucoma, increased ocular pressure, pruritus, rash, and hypersensitivity.

8 USE IN SPECIFIC POPULATIONS

8.1 Pregnancy

Teratogenic Effects: Pregnancy Category C

There are no adequate and well-controlled studies of triamcinolone acetonide nasal spray in pregnant women. Triamcinolone acetonide was teratogenic in rats, rabbits, and monkeys. Triamcinolone acetonide nasal spray, like other corticosteroids, should be used during pregnancy only if the potential benefit justifies the potential risk to the fetus. Since their introduction, experience with oral corticosteroids in pharmacologic as opposed to physiologic doses suggests that rodents are more prone to teratogenic effects from corticosteroids than humans. In addition, because there is a natural increase in glucocorticoid production during pregnancy, most women will require a lower exogenous corticosteroid dose and many will not need corticosteroid treatment during pregnancy.

In reproduction studies in rats and rabbits, triamcinolone acetonide administered by inhalation produced cleft palate and/or internal hydrocephaly and axial skeletal defects at exposures less than and 2 times, respectively, the maximum recommended daily intranasal dose in adults on a mcg/m^2 basis. In a monkey reproduction study, triamcinolone acetonide administered by inhalation produced cranial malformations at an exposure approximately 37 times the maximum recommended daily intranasal dose in adults on a mcg/m^2 basis.

8.3 Nursing Mothers

It is not known whether triamcinolone acetonide is excreted in human milk. Because other corticosteroids are excreted in human milk, caution should be exercised when triamcinolone acetonide nasal spray is administered to nursing women.

8.4 Pediatric Use

The safety and effectiveness of triamcinolone acetonide nasal spray has been evaluated in 518 children 6 to 12 years of age, and 176 adolescents 12 to 17 years of age [see Clinical Studies (14)]. The safety and effectiveness of triamcinolone acetonide nasal spray in children below 2 years of age have not been established.

Labeling describing use of triamcinolone acetonide nasal spray in pediatric patients 2 to 5 years of age is approved for Sanofi-Aventis U.S. Inc.’s Nasacort® AQ Nasal Spray. However, due to Sanofi-Aventis U.S. Inc.’s marketing exclusivity rights, a description of that use is not approved for this triamcinolone acetonide nasal spray labeling.

Controlled clinical studies have shown that intranasal corticosteroids may cause a reduction in growth velocity in pediatric patients. This effect has been observed in the absence of laboratory evidence of HPA axis suppression, suggesting that growth velocity is a more sensitive indicator of systemic corticosteroid exposure in pediatric patients than some commonly used tests of HPA axis function. The long-term effects of reduction in growth velocity associated with intranasal corticosteroids, including the impact of final adult height are unknown. The potential for “catch-up” growth following discontinuation of treatment with intranasal corticosteroids has not been adequately studied. The growth of pediatric patients receiving intranasal corticosteroids, including triamcinolone acetonide nasal spray, should be monitored routinely (e.g., via stadiometry). The potential growth effects of prolonged treatment should be weighed against the clinical benefits obtained and the risks/benefits of treatment alternatives. To minimize the systemic effects of intranasal corticosteroids, including triamcinolone acetonide nasal spray, each patient’s dose should be titrated to the lowest dosage that effectively controls his/her symptoms.

The potential for triamcinolone acetonide nasal spray to cause growth suppression in susceptible patients and when given at higher than recommended dosages cannot be ruled out.

8.5 Geriatric Use

Clinical studies of triamcinolone acetonide did not include sufficient numbers of subjects aged 65 and over to determine whether they respond differently from younger subjects. Other reported clinical experience has not identified differences in responses between the elderly and younger patients. In general, dose selection for an elderly patient should be cautious, usually starting at the low end of the dosing range, reflecting the greater frequency of decreased hepatic, renal, or cardiac function, and of concomitant disease or other drug therapy.

10 OVERDOSAGE

Chronic overdosage may result in signs/symptoms of hypercorticism [see Warnings and Precautions (5.4)]. There are no data on the effects of acute or chronic overdosage with triamcinolone acetonide nasal spray. Because of low systemic bioavailability and an absence of acute drug-related systemic findings in clinical studies overdose is unlikely to require any therapy other than observation.

Acute overdosing with the intranasal dosage form is unlikely in view of the total amount of active ingredient present and low bioavailability of triamcinolone acetonide. In the event that the entire contents of the bottle were administered all at once, via either oral or nasal application, clinically significant systemic adverse events would most likely not result.

11 DESCRIPTION

Triamcinolone acetonide, USP, the active ingredient in Triamcinolone Acetonide Nasal Spray, is a corticosteroid with the chemical designation 9-Fluoro-11ß,16α,17,21-tetrahydroxypregna-1,4-diene-3,20-dione cyclic 16,17-acetal with acetone.

C24H31FO6 M.W. 434.51

Triamcinolone Acetonide Nasal Spray is a thixotropic, water-based, metered-dose pump spray formulation unit containing a microcrystalline suspension of triamcinolone acetonide in an aqueous medium. Inactive ingredients are benzalkonium chloride, carboxymethylcellulose sodium, dextrose anhydrous, edetate disodium dihydrate, microcrystalline cellulose and polysorbate 80. Hydrochloric acid or sodium hydroxide may be added to adjust the pH to a target of 5.0 within a range of 4.5 and 6.0.

12 CLINICAL PHARMACOLOGY

12.1 Mechanism of Action

Triamcinolone acetonide is a synthetic fluorinated corticosteroid with approximately 8 times the potency of prednisone in animal models of inflammation.

Although the precise mechanism of corticosteroid antiallergic action is unknown, corticosteroids have been shown to have a wide range of actions on multiple cell types (e.g., mast cells, eosinophils, neutrophils, macrophages, lymphocytes) and mediators (e.g., histamine, eicosanoids, leukotrienes, cytokines) involved in inflammation.

12.2 Pharmacodynamics

In order to determine if systemic absorption plays a role in the effect of triamcinolone acetonide nasal spray on allergic rhinitis symptoms, a two week double-blind, placebo-controlled clinical study was conducted comparing triamcinolone acetonide, orally ingested triamcinolone acetonide, and placebo in 297 adult patients with seasonal allergic rhinitis. The study demonstrated that the therapeutic efficacy of triamcinolone acetonide nasal spray can be attributed to the topical effects of triamcinolone acetonide.

Adrenal Function

In order to evaluate the effects of systemic absorption on the Hypothalamic-Pituitary-Adrenal (HPA) axis, 3 clinical studies, one each in adults and in children 6 to 12 years of age and 2 to 5 years of age, were conducted.

The adult clinical study compared 220 mcg or 440 mcg triamcinolone acetonide per day, or 10 mg prednisone per day with placebo for 42 days. Adrenal response to a six-hour 250 mcg cosyntropin stimulation test showed that triamcinolone acetonide administered at doses of 220 mcg and 440 mcg had no statistically significant effect on HPA activity versus placebo. Conversely, oral prednisone at 10 mg/day significantly reduced the response to ACTH.

A study evaluating plasma cortisol response thirty and sixty minutes after 250 mcg cosyntropin stimulation in 80 pediatric patients 6 to 12 years of age who received 220 mcg or 440 mcg (twice the maximum recommended daily dose) daily for six weeks was conducted. No abnormal response to cosyntropin infusion (peak serum cortisol <18 mcg/dL) was observed in any pediatric patient after six weeks of dosing with triamcinolone acetonide at 440 mcg per day.

In pediatric patients 2 to 5 years of age, HPA axis assessment was performed; however, the results were inconclusive and an effect of triamcinolone acetonide nasal spray on adrenal function in children 2 to 5 years of age cannot be ruled out.

12.3 Pharmacokinetics

Based upon intravenous dosing of triamcinolone acetonide phosphate ester in adults, the half-life of triamcinolone acetonide was reported to be 88 minutes. The volume of distribution (Vd) reported was 99.5 L (SD ± 27.5) and clearance was 45.2 L/hour (SD ± 9.1) for triamcinolone acetonide. The plasma half-life of corticosteroids does not correlate well with the biologic half-life.

Pharmacokinetic characterization of the triamcinolone acetonide nasal spray formulation was determined in both normal adult subjects and patients with allergic rhinitis. Single dose intranasal administration of 220 mcg of triamcinolone acetonide nasal spray in normal adult subjects and patients demonstrated minimal absorption of triamcinolone acetonide. The mean peak plasma concentration was approximately 0.5 ng/mL (range: 0.1 to 1 ng/mL) and occurred at 1.5 hours post dose. The mean plasma drug concentration was less than 0.06 ng/mL at 12 hours, and below the assay detection limit (the minimum LOQ of the assay was 0.025 ng/mL) at 24 hours. The average terminal half-life was 3.1 hours. The range of mean AUC0–∞ values was 1.4 ng•hr/mL to 4.7 ng•hr/mL between doses of 110 mcg to 440 mcg in both patients and healthy volunteers. Dose proportionality was demonstrated in both normal adult subjects and in allergic rhinitis patients following single intranasal doses of 110 mcg or 220 mcg triamcinolone acetonide nasal spray. The Cmax and AUC0-∞ of the 440 mcg dose increased less than proportionally when compared to 110 and 220 mcg doses.

Following multiple dose administration of triamcinolone acetonide 440 mcg once daily in pediatric patients 6 to 12 years of age, plasma drug concentrations, AUC0-∞, Cmax and Tmax were similar to those values observed in adult patients receiving the same dose.

Labeling describing additional pharmacokinetics in pediatric patients 2 to 5 years of age treated with triamcinolone acetonide nasal spray is approved for Sanofi-Aventis U.S. Inc.’s Nasacort® AQ Nasal Spray. However, due to Sanofi-Aventis U.S. Inc.’s marketing exclusivity rights, a description of that pharmacokinetic information is not approved for this triamcinolone acetonide nasal spray labeling.

In animal studies using rats and dogs, three metabolites of triamcinolone acetonide have been identified. They are 6β-hydroxytriamcinolone acetonide, 21-carboxytriamcinolone acetonide and 21-carboxy-6β-hydroxytriamcinolone acetonide. All three metabolites are expected to be substantially less active than the parent compound due to (a) the dependence of anti-inflammatory activity on the presence of a 21-hydroxyl group, (b) the decreased activity observed upon 6-hydroxylation, and (c) the markedly increased water solubility favoring rapid elimination. There appeared to be some quantitative differences in the metabolites among species. No differences were detected in metabolic pattern as a function of route of administration.

13 NONCLINICAL TOXICOLOGY

13.1 Carcinogenesis, Mutagenesis, Impairment of Fertility

In a two-year study in rats, triamcinolone acetonide caused no treatment-related carcinogenicity at oral doses up to 1 mcg/kg (less than the maximum recommended daily intranasal dose in adults and children on a mcg/m^2 basis, respectively). In a two-year study in mice, triamcinolone acetonide caused no treatment-related carcinogenicity at oral doses up to 3 mcg/kg (less than the maximum recommended daily intranasal dose in adults and children on a mcg/m^2 basis, respectively).

No evidence of mutagenicity was detected from in vitro tests (a reverse mutation test in Salmonella bacteria and a forward mutation test in Chinese hamster ovary cells) conducted with triamcinolone acetonide.

In male and female rats, triamcinolone acetonide caused no change in pregnancy rate at oral doses up to 15 mcg/kg (less than the maximum recommended daily intranasal dose in adults on a mcg/m^2 basis). Triamcinolone acetonide caused increased fetal resorptions and stillbirths and decreases in pup weight and survival at doses of 5 mcg/kg and above (less than the maximum recommended daily intranasal dose in adults on a mcg/m^2 basis). At 1 mcg/kg (less than the maximum recommended daily intranasal dose in adults on a mcg/m^2 basis), it did not induce the above mentioned effects.

13.2 Animal Toxicology and/or Pharmacology

Triamcinolone acetonide was teratogenic in rats, rabbits, and monkeys. In rats, triamcinolone acetonide was teratogenic at inhalation doses of 20 mcg/kg and above (approximately 7/10 of the maximum recommended daily intranasal dose in adults on a mcg/m^2 basis). In rabbits, triamcinolone acetonide was teratogenic at inhalation doses of 20 mcg/kg and above (approximately 2 times the maximum recommended daily intranasal dose in adults on a mcg/m^2 basis). In monkeys, triamcinolone acetonide was teratogenic at an inhalation dose of 500 mcg/kg (approximately 37 times the maximum recommended daily intranasal dose in adults on a mcg/m^2 basis). Dose-related teratogenic effects in rats and rabbits included cleft palate and/or internal hydrocephaly and axial skeletal defects, whereas the effects observed in the monkey were cranial malformations.

Hypoadrenalism may occur in infants born of mothers receiving corticosteroids during pregnancy. Such infants should be carefully observed.

14 CLINICAL STUDIES

The safety and efficacy of triamcinolone acetonide nasal spray have been evaluated in 10 double-blind, placebo-controlled clinical studies of two- to four-weeks duration in adults and children 12 years and older with seasonal or perennial allergic rhinitis. The number of patients treated with triamcinolone acetonide nasal spray in these studies was 1266; of these patients, 675 were males and 591 were females.

Overall, the results of these clinical studies in adults and children 12 years and older demonstrated that triamcinolone acetonide nasal spray 220 mcg once daily (2 sprays in each nostril), when compared to placebo, provides statistically significant relief of nasal symptoms of seasonal or perennial allergic rhinitis including sneezing, stuffiness, discharge, and itching.

The safety and efficacy of triamcinolone acetonide nasal spray, at doses of 110 mcg or 220 mcg once daily, have also been adequately studied in two double-blind, placebo-controlled studies of two- and twelve-weeks duration in children ages 6 through 12 years with seasonal and perennial allergic rhinitis. These studies included 341 males and 177 females. Triamcinolone acetonide administered at either dose resulted in statistically significant reductions in the severity of nasal symptoms of allergic rhinitis.

Labeling describing additional clinical studies of triamcinolone acetonide nasal spray in pediatric patients 2 to 5 years of age is approved for Sanofi-Aventis U.S. Inc.’s Nasacort® AQ Nasal Spray. However, due to Sanofi-Aventis U.S. Inc.’s marketing exclusivity rights, a description of those clinical studies is not approved for this triamcinolone acetonide nasal spray labeling.

16 HOW SUPPLIED/STORAGE AND HANDLING

16.1 How Supplied

Triamcinolone Acetonide Nasal Spray, 55 mcg per spray, is supplied in a white high-density polyethylene container with a metered-dose pump unit, white nasal adapter, and patient instructions.

The contents of one 16.5 gram bottle provide 120 actuations. After 120 actuations, the amount of triamcinolone acetonide delivered per actuation may not be consistent and the unit should be discarded. Each actuation delivers 55 mcg triamcinolone acetonide from the nasal actuator after an initial priming of 5 sprays [see Administration Information (2.3)].

In the Patient Package Information, patients are provided with a check-off form to track usage [see Patient Counseling Information (17)].

WARNING: KEEP THIS AND ALL MEDICATIONS OUT OF THE REACH OF CHILDREN.

Rx only

16.2 Storage

Store at 20° to 25°C (68° to 77°F) [See USP Controlled Room Temperature].

17 PATIENT COUNSELING INFORMATION

See FDA-Approved Patient Labeling accompanying the product.

17.1 Local Nasal Effects

Patients should be informed that treatment with triamcinolone acetonide nasal spray may lead to adverse reactions, which include epistaxis and nasal ulceration. Candida infection may also occur with treatment with triamcinolone acetonide nasal spray. In addition, nasal corticosteroids are associated with nasal septal perforation and impaired wound healing. Patients who have experienced recent nasal ulcers, nasal surgery, or nasal trauma should not use triamcinolone acetonide nasal spray until healing has occurred [see Warnings and Precautions (5.1)].

17.2 Cataracts and Glaucoma

Patients should be informed that glaucoma and cataracts are associated with nasal and inhaled corticosteroid use. Patients should inform his/her healthcare provider if a change in vision is noted while using triamcinolone acetonide nasal spray [see Warnings and Precautions (5.2)].

17.3 Immunosuppression

Patients who are on immunosuppressant doses of corticosteroids should be warned to avoid exposure to chickenpox or measles and, if exposed, to consult their physician without delay. Patients should be informed of potential worsening of existing tuberculosis, fungal, bacterial, viral or parasitic infections, or ocular herpes simplex [see Warnings and Precautions (5.3)].

17.4 Use Daily for Best Effect

Patients should use triamcinolone acetonide nasal spray on a regular once-daily basis for optimal effect. It is also important to shake the bottle well before each use. Do not blow your nose for 15 minutes after using the spray. Triamcinolone acetonide nasal spray, like other corticosteroids, does not have an immediate effect on rhinitis symptoms. Although improvement in some patient symptoms may be seen within the first day of treatment, maximum benefit may not be reached for up to one week. The patient should not increase the prescribed dosage but should contact the physician if symptoms do not improve or if the condition worsens.

17.5 Keep Spray Out of Eyes

Patients should be informed to avoid spraying triamcinolone acetonide nasal spray in their eyes.

17.6 Patient Package Information

IMPORTANT: Please read these instructions carefully before using your triamcinolone acetonide nasal spray.

Manufactured In Israel By:

Perrigo Israel Pharmaceuticals Ltd.

Industrial Zone, Yeruham 80500, Israel

Manufactured For:

TEVA PHARMACEUTICALS USA

Sellersville, PA 18960

Iss. 10/2010

TRIAMCINOLONE ACETONIDE
Nasal Spray

Patient Information

These instructions provide important information about triamcinolone acetonide. Ask your healthcare provider or pharmacist if you have any questions.

Important: For use as a nasal spray only.

What is Triamcinolone Acetonide?

Triamcinolone acetonide nasal spray is a prescription medicine called a corticosteroid used to treat nasal symptoms of seasonal and year around allergies in adults and children 6 years of age and older. When triamcinolone acetonide is sprayed in your nose, this medicine helps to lessen the symptoms of sneezing, runny nose, nasal itching and stuffy nose.

Triamcinolone acetonide is not for children under the age of 2 years.

Who should use Triamcinolone Acetonide?

Do not use triamcinolone acetonide if you have had a reaction to triamcinolone acetonide or to any of the other ingredients in triamcinolone acetonide. See the end of this leaflet for a complete list of ingredients in triamcinolone acetonide.

What should I tell my healthcare provider before using Triamcinolone Acetonide?

Tell your healthcare provider if you are:

- pregnant or planning to become pregnant
- breast-feeding
- exposed to chickenpox or measles
- feeling unwell or have any symptoms that you do not understand

Tell your healthcare provider about all of the medicines you take, including prescription and non-prescription medicines, vitamins, and herbal supplements.

How do I use Triamcinolone Acetonide?

- Use triamcinolone acetonide exactly as your healthcare provider tells you.
- You will get the best results if you use triamcinolone acetonide regularly and without missing a dose. Do not take extra doses.
- Triamcinolone acetonide should be used as a nasal spray only. Do not spray it in your eyes or mouth.
- Your healthcare provider will tell you how and when to use triamcinolone acetonide. Do not use more triamcinolone acetonide or take it more often than your healthcare provider tells you.
- The prescription label will usually tell you how many sprays to take and how often. If it does not or if you are unsure, ask your healthcare provider or pharmacist.
  - For people aged 12 years and older, the usual dose is 2 sprays in each nostril, one time each day.
  - For children aged 6 to 12 years, the usual dose is 1 spray in each nostril, one time each day. Your healthcare provider may tell you to take 2 sprays in each nostril one time each day.
  - An adult should help a young child use this medicine.

Do not stop taking triamcinolone acetonide without telling your healthcare provider. Before you throw away triamcinolone acetonide, talk to your healthcare provider to see if you need another prescription. If your healthcare provider tells you to continue using triamcinolone acetonide, throw away the empty or expired bottle and use a new bottle of triamcinolone acetonide.

- For detailed instructions, see the “Patient Instructions for Use” at the end of this leaflet.
- Some symptoms may get better on the first day of treatment. It generally takes one week of use to feel the most benefit.
- Protect your eyes from the spray. If you get the spray in your eyes, rinse your eyes well with water.
- If your symptoms do not improve, or if they become worse, contact your healthcare provider.
- Tell your healthcare provider if you have irritation, burning or stinging inside your nose that does not go away when using triamcinolone acetonide.

What are the possible side effects of Triamcinolone Acetonide?

Common side effects of triamcinolone acetonide include:

Sore throat, headache, and nosebleeds. If you have an increase in nosebleeds after using triamcinolone acetonide or the inside of your nose hurts, contact your healthcare provider.

Tell your healthcare provider if you have any side effect that bothers you or that does not go away. Call your doctor for medical advice about side effects. You may report side effects to the FDA at 1-800-FDA-1088.

Patient Instructions for Use

Read these instructions carefully before using your triamcinolone acetonide.

Before using the spray pump bottle:

1. Pull the cover and the clip off the spray pump unit. See figure A.
  If the top part of the spray pump comes off of the bottle when removing the cover, then re-insert the stem back into the pump.
2. Figure A
3. Shake the spray pump bottle before each use.
  Priming the Spray Pump Bottle
4. Before using the spray pump bottle for the first time, it must be primed. To prime, put your thumb on the bottom of the bottle and your index and middle fingers on the “shoulders” of the bottle, and hold it upright. See figure B.
5. Figure B
6. Point the bottle away from your eyes. Push the bottle up with your thumb and against your two fingers firmly and quickly until a fine spray appears. Do this pumping action 5 times.
  Now your spray pump bottle is primed and ready for use.
  A fine mist can only be made by a rapid and firm pumping action.
7. Repeat priming the pump, if it has not been used for more than 2 weeks. To reprime, shake the spray pump bottle and pump it just one time. Now the spray pump bottle is reprimed.
  Using the spray:
8. Gently blow your nose to clear it, if needed. For small children, be sure to help them gently blow their nose, as much as possible.
9. Pull off the cover and clip as shown in figure C. Shake the spray pump well.
10. Figure C
11. Hold the spray pump firmly, with the index and middle finger on either side of the spray tip. Place your thumb on the bottom of the bottle. Be careful so that your fingers will not slip off the spray pump as you spray inside your nose. See figure D.
12. Figure D
13. Put the spray tip into one side of your nose. The tip should not reach far into the nose. Rest the side of your index finger against your upper lip. Tip your head back a little and aim the spray toward the back of your nose. See figure E.
14. Figure E
15. Press against the other side of your nose with your finger so the nostril is closed. Pump the spray bottle by pushing on the bottom of the bottle with your thumb firmly and quickly for the full dose of medicine. Sniff gently at the same time to help the medicine get to the back of your nose. See figure F. Repeat this step for the other side.
16. Figure F
17. Repeat steps 8, 9 and 10 if your healthcare provider tells you to use more than one spray in each nostril.
18. Do not blow your nose for 15 minutes after using the spray.
19. After use, wipe the nozzle on the spray bottle with a clean tissue, and replace the blue cover.
20. Keep the cover and the clip on the spray pump bottle when not in use.
  Cleaning the spray pump bottle:
21. To clean the spray pump bottle, remove the cover and the spray nozzle only. Soak the cover and spray nozzle in warm water for a few minutes, and then rinse under cold water. See figure G.
22. Figure G
23. Shake or tap off the excess water and allow to air dry. Once the cap and spray nozzle are dry, put the nozzle back onto the bottle, and prime the bottle as necessary until a fine mist is made. Use the spray as directed by your healthcare provider.
  If the spray bottle does not work:
  The hole in the tip of the nozzle may be blocked. Never try to unblock the spray hole or enlarge it with a pin or other sharp object. This will make the spray mechanism not work correctly. Changing the size of the opening can change the amount of medicine you or your child will receive. This could cause an overdose of the medicine. To clean nasal spray pump bottle, refer to Step 15.
  Important information
  Repriming the spray pump is only necessary when it has not been used for more than 2 weeks. To reprime, shake the bottle and only pump the spray bottle one time. Do not reprime if you use the spray more often than every two weeks.
  Each triamcinolone acetonide bottle contains 120 doses of medicine plus a little extra for priming the pump. A check-off chart is included with your triamcinolone acetonide to help you keep track of the number of sprays. This will help make sure that you receive 120 sprays of triamcinolone acetonide.

How should I store Triamcinolone Acetonide?

- Store triamcinolone acetonide between 68° to 77°F (20° to 25° C).
- After using 120 sprays, throw the medicine away, as directed by your healthcare provider, even if the bottle is not empty. You may not get enough medicine if you use the bottle after 120 sprays.

Keep triamcinolone acetonide and all medicines out of the reach of children.

General information about the safe and effective use of triamcinolone acetonide.

Medicines are sometimes prescribed for conditions that are not mentioned in patient information. Do not use triamcinolone acetonide for a condition for which it was not prescribed. Do not give triamcinolone acetonide to other people, even if they have the same symptoms that you have. It may harm them.

This leaflet summarizes the most important information about triamcinolone acetonide. If you would like more information, talk with your healthcare provider. You can ask your pharmacist or healthcare provider for information about triamcinolone acetonide that is written for health professionals.

For more information, call 1-800-227-7522.

What are the ingredients in Triamcinolone Acetonide Nasal Spray?

Active ingredient: triamcinolone acetonide

Inactive ingredients: benzalkonium chloride, carboxymethylcellulose sodium, dextrose anhydrous, edetate disodium dihydrate, microcrystalline cellulose and polysorbate 80. Hydrochloric acid or sodium hydroxide may be added to adjust the pH to a target of 5.0 within a range of 4.5 and 6.0.

Labeling describing the use of triamcinolone acetonide nasal spray in pediatric patients 2 to 5 years of age is approved for Sanofi-Aventis U.S. Inc.’s Nasacort® AQ Nasal Spray. However, due to Sanofi-Aventis U.S. Inc.’s marketing exclusivity rights, a description of that use is not approved for this triamcinolone acetonide nasal spray labeling.

Manufactured In Israel By:

Perrigo Israel Pharmaceuticals Ltd.

Industrial Zone, Yeruham 80500, Israel

Manufactured For:

TEVA PHARMACEUTICALS USA

Sellersville, PA 18960

Iss. 10/2010

11001739